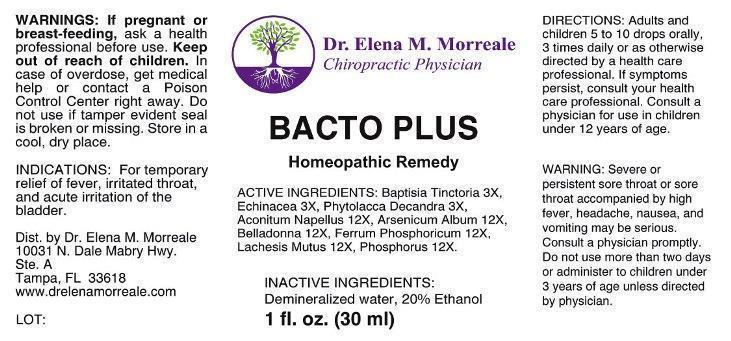 DRUG LABEL: Bacto Plus
NDC: 50813-0006 | Form: LIQUID
Manufacturer: Dr. Elena M. Morreale
Category: homeopathic | Type: HUMAN OTC DRUG LABEL
Date: 20150121

ACTIVE INGREDIENTS: BAPTISIA TINCTORIA ROOT 3 [hp_X]/1 mL; ECHINACEA ANGUSTIFOLIA 3 [hp_X]/1 mL; PHYTOLACCA AMERICANA ROOT 3 [hp_X]/1 mL; ACONITUM NAPELLUS 12 [hp_X]/1 mL; ARSENIC TRIOXIDE 12 [hp_X]/1 mL; ATROPA BELLADONNA 12 [hp_X]/1 mL; FERRUM PHOSPHORICUM 12 [hp_X]/1 mL; LACHESIS MUTA VENOM 12 [hp_X]/1 mL; PHOSPHORUS 12 [hp_X]/1 mL
INACTIVE INGREDIENTS: WATER; ALCOHOL

Drug Facts:

ACTIVE INGREDIENTS:

Baptisia tinctoria 3X, Echinacea (Angustifolia) 3X, Phytolacca decandra 3X, Aconitum napellus 12X, Arsenicum album 12X, Belladonna 12X, Ferrum phosphoricum 12X, Lachesis mutus 12X, Phosphorus 12X.

INDICATIONS:

For temporary relief of fever, irritated throat, and acute irritation of the bladder.

WARNINGS:

If pregnant or breast-feeding, ask a health professional before use.

Keep out of reach of children. In case of overdose, get medical help or contact a Poison Control Center right away.

Do not use if tamper evident seal is broken or missing.

Store in a cool, dry place.

WARNING: Severe or persistent sore throat or sore throat accompanied by high fever, headache, nausea, and vomiting may be serious. Consult a physician promptly. Do not use more than two days or administer to children under 3 years of age unless directed by physician.

Keep out of reach of children. In case of overdose, get medical help or contact a Poison Control Center right away.

DIRECTIONS:

Adults and children 5 to 10 drops orally, 3 times daily or as otherwise directed by a health care professional. If symptoms persist, consult your health care professional. Consult a physician for use in children under 12 years of age.

INDICATIONS:

For temporary relief of fever, irritated throat, and acute irritation of the bladder.

INACTIVE INGREDIENTS:

Demineralized Water, 20% Ethanol

QUESTIONS:

Dist. by Dr. Elena M. Morreale

10031 N. Dale Mabry Hwy.

Ste. A

Tampa, FL 33618

www.drelenamorreale.com

PACKAGE LABEL DISPLAY:

Dr. Elena M. Morreale

Chiropractic Physician

BACTO PLUS

Homeopathic Remedy

1 fl. oz. (30 ml)